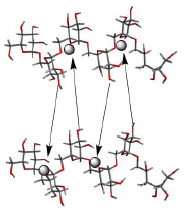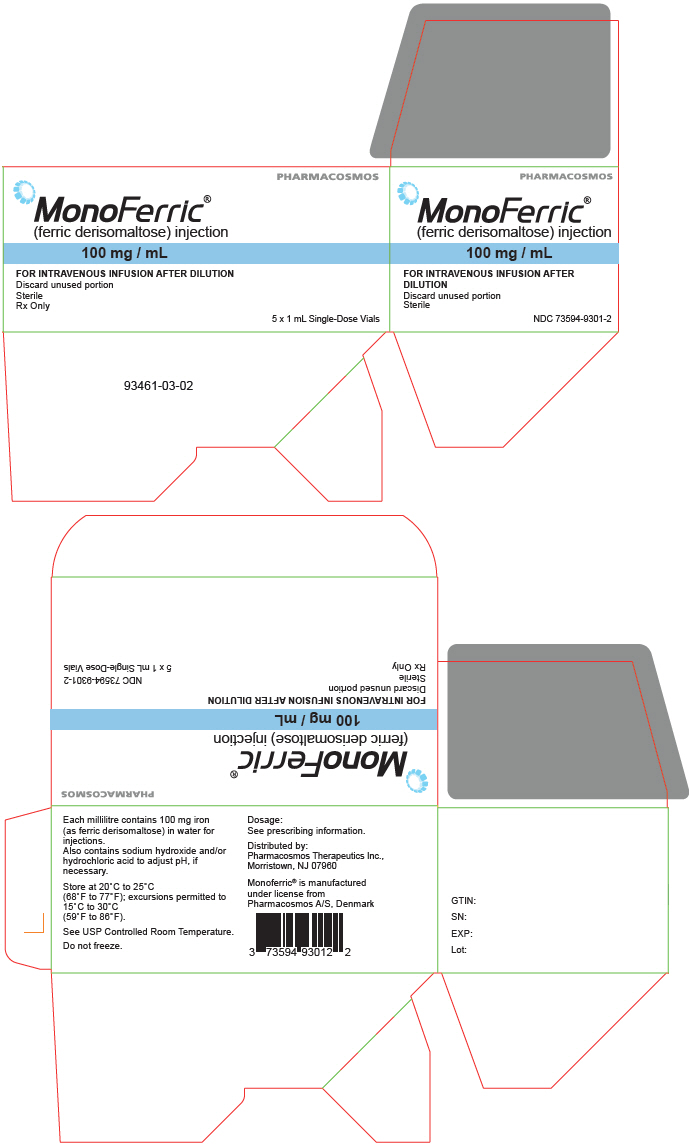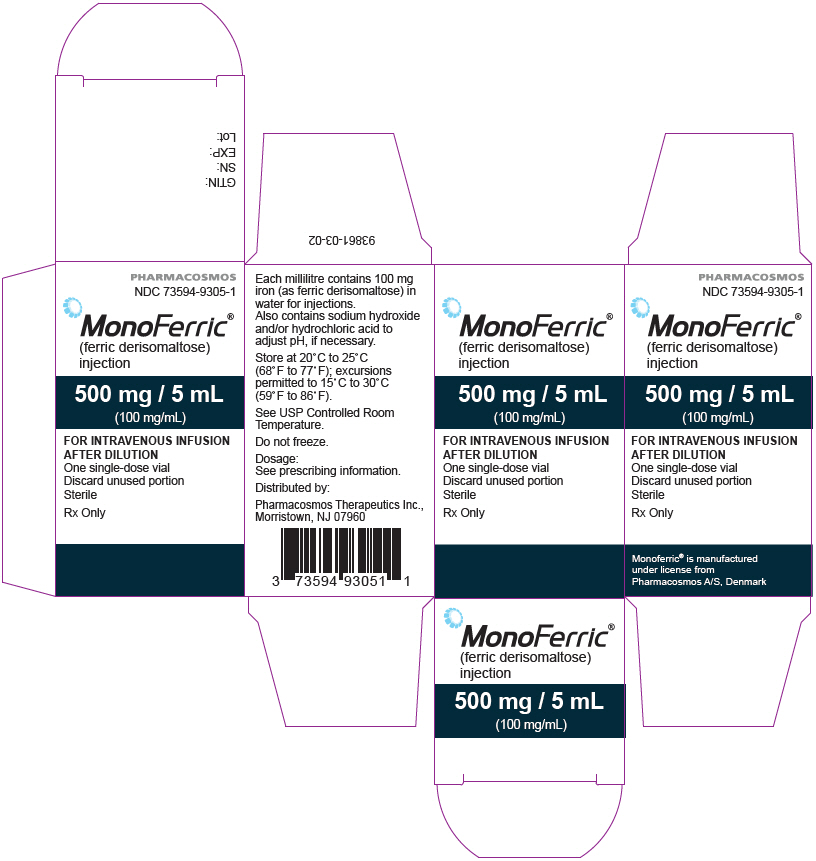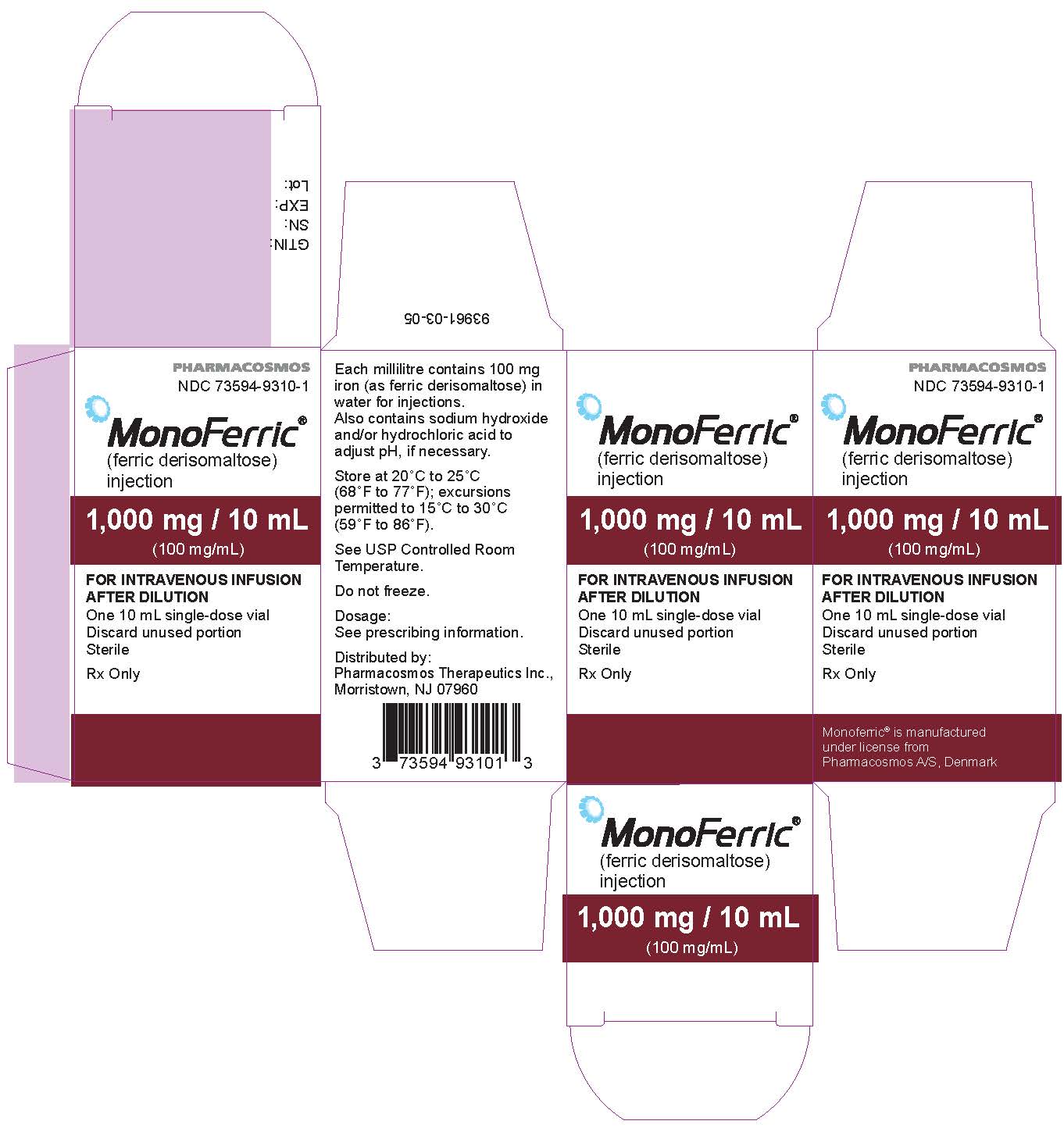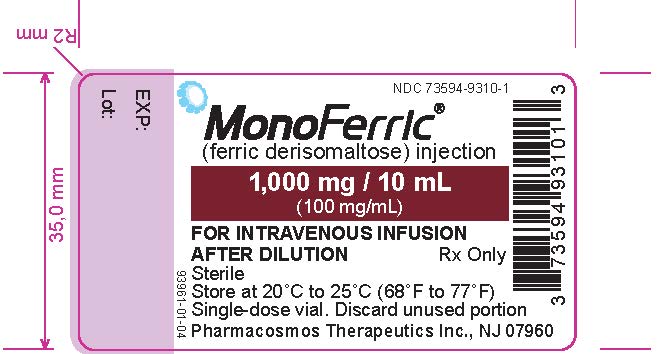 DRUG LABEL: Monoferric
NDC: 73594-9301 | Form: INJECTION, SOLUTION
Manufacturer: Pharmacosmos Therapeutics Inc.
Category: prescription | Type: HUMAN PRESCRIPTION DRUG LABEL
Date: 20251125

ACTIVE INGREDIENTS: FERRIC DERISOMALTOSE 100 mg/1 mL
INACTIVE INGREDIENTS: HYDROCHLORIC ACID; SODIUM HYDROXIDE; WATER; NITROGEN

HIGHLIGHTS OF PRESCRIBING INFORMATION

These highlights do not include all the information needed to use MONOFERRIC safely and effectively. See Full Prescribing Information for MONOFERRIC.
MONOFERRIC (ferric derisomaltose) injection, for intravenous use
Initial U.S. Approval: 2020

1 INDICATIONS AND USAGE

MONOFERRIC is an iron replacement product indicated for the treatment of iron deficiency anemia in adult patients:

- who have intolerance to oral iron or have had unsatisfactory response to oral iron. (1)
- who have non-hemodialysis dependent chronic kidney disease. (1)

2 DOSAGE AND ADMINISTRATION

- For patients weighing 50 kg or more: Administer 1,000 mg of Monoferric as an intravenous infusion.
- For patients weighing less than 50 kg: Administer Monoferric as 20 mg/kg actual body weight as an intravenous infusion.
- Repeat Monoferric treatment if iron deficiency anemia reoccurs. (2)

3 DOSAGE FORMS AND STRENGTHS

- Injection: 1,000 mg iron /10 mL (100 mg/mL) single-dose vial (3)
- Injection: 500 mg iron/5 mL (100 mg/mL) single-dose vial (3)
- Injection: 100 mg iron/mL single-dose vial (3)

4 CONTRAINDICATIONS

Serious hypersensitivity to Monoferric or any of its components. (4)

5 WARNINGS AND PRECAUTIONS

- Hypersensitivity Reactions: Monitor patients for signs and symptoms of hypersensitivity during and after Monoferric administration for at least 30 minutes and until clinically stable following completion of the infusion. (5.1)
- Iron Overload: Do not administer Monoferric to patients with iron overload. (5.2)

6 ADVERSE REACTIONS

Most commonly reported adverse reactions (incidence ≥1%) are rash and nausea. (6)

To report SUSPECTED ADVERSE REACTIONS, contact Pharmacosmos at 1-888-828-0655 or FDA at 1-800-FDA-1088 or www.fda.gov/medwatch.

FULL PRESCRIBING INFORMATION

1 INDICATIONS AND USAGE

Monoferric is indicated for the treatment of iron deficiency anemia (IDA) in adult patients:

- who have intolerance to oral iron or have had unsatisfactory response to oral iron
- who have non-hemodialysis dependent chronic kidney disease (NDD-CKD)

2 DOSAGE AND ADMINISTRATION

2.1 Recommended Dosage

For patients weighing 50 kg or more: Administer 1,000 mg of Monoferric by intravenous infusion over at least 20 minutes as a single dose. Repeat dose if iron deficiency anemia reoccurs.

For patients weighing less than 50 kg: Administer Monoferric as 20 mg/kg actual body weight by intravenous infusion over at least 20 minutes as a single dose. Repeat dose if iron deficiency anemia reoccurs.

The dosage of Monoferric is expressed in mg of elemental iron. Each mL of Monoferric contains 100 mg of elemental iron.

Only administer Monoferric when personnel and therapies are immediately available for the treatment of serious hypersensitivity reactions (Warnings and Precautions (5.1)) .

2.2 Preparation and Administration

Inspect parenteral drug products visually for the absence of particulate matter and discoloration prior to administration. The product contains no preservatives.

Each vial of Monoferric is single-dose only. Discard unused portion.

- Withdraw the appropriate volume of Monoferric and dilute in 100 mL to 500 mL of 0.9% Sodium Chloride Injection, USP.
- Final diluted concentration should be more than 1 mg iron/mL.
- Compatibility of Monoferric with other drugs has not been established. Monoferric should not be mixed with or physically added to solutions containing other drugs.
- Administer the prepared solution via intravenous infusion over at least 20 minutes.
- Following dilution with 0.9% Sodium Chloride Injection, USP, Monoferric solution may be stored at room temperature for up to 8 hours.
- Extravasation of Monoferric may cause brown discoloration at the extravasation site which may be long lasting. Monitor for extravasation. If extravasation occurs, discontinue the Monoferric administration at that site.

3 DOSAGE FORMS AND STRENGTHS

Monoferric is a sterile, dark brown, non-transparent aqueous solution available as:

- Injection: 1,000 mg iron/10 mL (100 mg/mL) single-dose vial
- Injection: 500 mg iron/5 mL (100 mg/mL) single-dose vial
- Injection: 100 mg iron/mL single-dose vial

4 CONTRAINDICATIONS

Monoferric is contraindicated in patients with a history of serious hypersensitivity to Monoferric or any of its components (see Warnings and Precautions (5.1), Description (11)) . Reactions have included shock, clinically significant hypotension, loss of consciousness, and/or collapse.

5 WARNINGS AND PRECAUTIONS

5.1 Hypersensitivity Reactions

Serious hypersensitivity reactions, including anaphylactic-type reactions, some of which have been life-threatening and fatal, have been reported in patients receiving Monoferric. Patients may present with shock, clinically significant hypotension, loss of consciousness, and/or collapse. Monitor patients for signs and symptoms of hypersensitivity during and after Monoferric administration for at least 30 minutes and until clinically stable following completion of the infusion. Only administer Monoferric when personnel and therapies are immediately available for the treatment of serious hypersensitivity reactions. Monoferric is contraindicated in patients with prior serious hypersensitivity reactions to Monoferric or any of its components (see Contraindications (4)). In clinical trials in patients with IDA and CKD, serious or severe hypersensitivity were reported in 0.3% (6/2008) of the Monoferric treated subjects. These included 3 events of hypersensitivity in 3 patients; 2 events of infusion-related reactions in 2 patients and 1 event of asthma in one patient.

5.2 Iron Overload

Excessive therapy with parenteral iron can lead to excess iron storage and possibly iatrogenic hemosiderosis or hemochromatosis. Monitor the hematologic response (hemoglobin and hematocrit) and iron parameters (serum ferritin and transferrin saturation) during parenteral iron therapy. Do not administer Monoferric to patients with iron overload (see Overdosage (10)) .

6 ADVERSE REACTIONS

The following clinically significant adverse reactions are discussed in greater detail in other sections of the labeling:

- Hypersensitivity Reactions (see Warnings and Precautions (5.1)) .
- Iron Overload (see Warnings and Precautions (5.2)) .

6.1 Clinical Trials Experience

Because clinical trials are conducted under widely varying conditions, the adverse reaction rates observed cannot be directly compared to rates in other clinical trials and may not reflect the rates observed in clinical practice.

The safety of Monoferric was evaluated in 3008 patients with iron deficiency anemia enrolled in two randomized, actively-controlled trials. Trial 1 enrolled adult patients with iron deficiency anemia with intolerance to oral iron or had an unsatisfactory response to oral iron with a clinical need for repletion of iron stores. Eligible subjects were required to have a baseline hemoglobin of ≤11g/dl, transferrin saturation (TSAT) of less than 20% and serum ferritin level of <100 ng/mL. Trial 2 enrolled adult patients with non-dialysis dependent chronic kidney disease (CKD) with iron deficiency anemia (see Clinical Studies (14)). Eligible subjects also had to have serum ferritin ≤100 ng/mL or ≤300 ng/mL if TSAT ≤30%.

Trial 1 and Trial 2

In the two randomized, actively-controlled clinical trials, Trial 1 and Trial 2 (see Clinical Studies (14)) , patients were randomized in a 2:1 ratio to intravenous Monoferric (n = 2008) or intravenous iron sucrose (n = 1000) respectively. Monoferric was administered as a single intravenous infusion of 1000 mg diluted in 100 mL 0.9 % sodium chloride and given over approximately 20 minutes (approximately 50 mg iron/min). Iron sucrose was administered as 200 mg undiluted intravenous injections over approximately 2-5 minutes and repeated according to standard practice or physician choice up to a maximum of five times (1000 mg) within the first two weeks starting at baseline.

The data described below reflect exposure to Monoferric in 2008 patients exposed to a 1000 mg single intravenous dose of Monoferric. The mean cumulative intravenous Iron exposure was 984 mg.

Trial 1 included 1483 patients with iron deficiency anemia in the safety analysis that had intolerance to oral iron or have had unsatisfactory response to oral iron or with a clinical need for rapid repletion of iron stores. Trial 2 included 1525 patients in the safety analysis who had non-dialysis dependent CKD. The mean (SD) age of the combined study population was 56.4 (18.3) years. The majority of patients were women (75.7%).

Adverse reactions were reported in 8.6% (172/2008) of patients treated with Monoferric.

Adverse reactions related to treatment and reported by ≥1% of the treated patients in the combined analysis of Trial 1 and 2 are listed in Table 1.

Table 1. Adverse Reactions (≥1%) in Patients Receiving Monoferric in Clinical Trials 1 and 2
 | Monoferric (N = 2008) N (%) | Iron sucrose (N = 1000) N (%)
Adverse Reaction
Nausea | 24 (1.2) | 11 (1.1)
Rash | 21 (1) | 1 (0.1)

Adjudicated serious or severe hypersensitivity reactions were reported in 6/2008 (0.3%) patients in the Monoferric group.

Hypophosphatemia (serum phosphate <2.0 mg/dL) was reported in 3.5% of Monoferric-treated patients in Trials 1 & 2.

6.2 Post-marketing Experience

Because these reactions are reported voluntarily from a population of uncertain size, it is not always possible to reliably estimate their frequency or establish a causal relationship to drug exposure. The following adverse reactions have been most commonly reported from the post-marketing spontaneous reports with Monoferric:

Cardiac disorders: Tachycardia

Gastrointestinal disorders: Abdominal pain, nausea and vomiting, constipation, diarrhea

General disorders and administration site conditions: Fatigue, pyrexia, chest pain, chills, Fishbane reaction, extravasation, influenza like symptoms, injection site reactions, malaise, pain

Immune System disorders: Anaphylactic/anaphylactoid reaction, hypersensitivity

Investigations: Hepatic enzymes increased

Musculoskeletal and connective tissue disorders: Back pain, muscle spasms, arthralgia, myalgia

Nervous system disorders: Dizziness, headache, paresthesia, dysgeusia, seizure, loss of consciousness, syncope

Psychiatric disorders: Anxiety

Respiratory, thoracic and mediastinal disorders: Dyspnea, cough, bronchospasm

Skin and subcutaneous tissue disorders: Erythema, urticaria, discoloration skin, rash, pruritus, skin exfoliation, angioedema, sweating

Vascular disorders: Hypertension, hypotension, flushing, phlebitis

Extravasation of Monoferric at the injection site that may lead to irritation of the skin and potentially long lasting brown discoloration at the site of injection has also been reported.

8 USE IN SPECIFIC POPULATIONS

8.1 Pregnancy

Risk Summary

There are no available data on Monoferric use in pregnant women to evaluate for a drug-associated risk of major birth defects, miscarriage or adverse maternal or fetal outcomes. Published studies on the use of intravenous iron products in pregnant women have not reported an association with adverse developmental outcomes. However, these studies cannot establish or exclude the absence of any drug-related risk during pregnancy because the studies were not designed to assess for the risk of major birth defects (see Data) . There are risks to the mother and fetus associated with untreated iron deficiency anemia (IDA) in pregnancy as well as risks to the fetus associated with maternal severe hypersensitivity reactions (see Clinical Considerations) . Iron complexes have been reported to be teratogenic and embryocidal in non-iron depleted pregnant animals. The findings in animals may be due to iron overload and may not be applicable to patients with iron deficiency. Animal reproduction studies of ferric derisomaltose administered to rats and rabbits during the period of organogenesis caused adverse developmental outcomes including structural abnormalities and embryo-fetal mortality at doses approximately 0.09 and 0.4 times the maximum recommended human dose (MRHD) of 1000 mg, respectively, based on body surface area (see Data) .

The estimated background risk of major birth defects and miscarriage for the indicated populations is unknown. Adverse outcomes in pregnancy occur regardless of the health of the mother or the use of medications. In the U.S. general population, the estimated background risk of major birth defects and miscarriage in clinically recognized pregnancies is 2-4% and 15-20%, respectively.

Clinical Considerations

Disease-associated maternal and/or embryo/fetal risk

Untreated iron deficiency anemia (IDA) in pregnancy is associated with adverse maternal outcomes such as post-partum anemia. Adverse pregnancy outcomes associated with IDA includes increased risk for preterm delivery and low birth weight.

Fetal/Neonatal adverse reactions

Severe adverse reactions including circulatory failure (severe hypotension, shock including in the context of anaphylactic reaction) may occur in pregnant women with parenteral iron products (such as Monoferric) which may cause fetal bradycardia, especially during the second and third trimester.

Data

Animal Data

Iron complexes have been reported to be teratogenic and embryocidal in non-anemic pregnant animals at single doses above 125 mg iron/kg body weight. The highest recommended dose in human clinical use is 20 mg iron/kg body weight.

In a combined fertility and embryo-fetal development study in rats, ferric derisomaltose was administered intravenously to female rats 14 days prior to cohabitation and through gestation day (GD) 17 at doses of 3, 11, and 32 mg Fe/kg/day. The doses of 11 and 32 mg Fe/kg/day (approximately 0.1 and 0.3 times the MRHD of 1000 mg, based on body surface area (BSA)) resulted in an increase in the incidence of skeletal developmental delays.

Ferric derisomaltose was administered intravenously to pregnant rabbits during organogenesis, from GD7 to GD20, at doses of 11, 25 and 43 mg Fe/kg/day. The dose of 43 mg Fe/kg/day (approximately 0.8 times the MRHD of 1000 mg, based on BSA) resulted in increased maternal mortality, abortion, and premature delivery, and increased postimplantation loss. Adverse developmental findings at this dose included fetal mortality, reduced fetal weights, and fetal developmental variations and malformations (including domed head, cleft palate, microglossia, hydrocephaly, small brain). Fetal malformations and reduced fetal weights were also noted in the 25 mg Fe/kg/day group (approximately 0.5 times the MRHD based on BSA).

8.2 Lactation

Risk Summary

The available data on the use of Monoferric in lactating women demonstrate that iron is present in breast milk. However, the data do not inform the potential exposure of iron for the breastfed child or the effects on milk production. The developmental and health benefits of breastfeeding should be considered along with the mother's clinical need for Monoferric in addition to any potential adverse effects on the breastfed child from the drug or from the underlying maternal condition.

Clinical Considerations

Monitor breastfed children for gastrointestinal toxicity (constipation, diarrhea).

8.4 Pediatric Use

Safety and effectiveness have not been established in pediatric patients.

8.5 Geriatric Use

Of the 3934 patients in clinical studies of Monoferric, 29% were 65 years and over, while 13% were 75 years and over. No overall differences in safety or effectiveness were observed between these patients and younger subjects, and other reported clinical experience has not identified differences in responses between the elderly and younger patients, but greater sensitivity of some older individuals cannot be ruled out.

10 OVERDOSAGE

Excessive dosages of Monoferric may lead to accumulation of iron in storage sites potentially leading to hemosiderosis and hemochromatosis. Avoid use of Monoferric in patients with iron overload (see Warnings and Precautions (5.2)) .

11 DESCRIPTION

Monoferric is an iron replacement product containing ferric derisomaltose for intravenous infusion. Ferric derisomaltose is an iron carbohydrate complex with a matrix structure composed of interchanging layers of ferric hydroxide and the carbohydrate derisomaltose. Derisomaltose consists of linear, hydrogenated isomaltooligosaccharides with an average molecular weight of 1000 Da and a narrow molecular weight distribution that is almost devoid of mono- and disaccharides.

Ferric derisomaltose has an average molecular weight of 155,000 Da and has the following empirical formula:

{FeO(1-3X) (OH)(1+3X) (C6H5O7^3-)X}, (H20)T, -

(C6H10O6)R(-C6H10O5-)Z(C6H13O5)R, (NaCl)Y

X = 0.0311; T = 0.25; R = 0.14; Z = 0.49; Y = 0.14

Iron atoms placed in the electronegative cavities of the 3-D structure between and within the derisomaltose molecules. A schematic representation is presented below

Monoferric is a sterile, dark brown, non-transparent aqueous solution with pH 5.0-7.0, containing ferric derisomaltose dissolved in water for injections and filled into Type I glass vials.

Each 1 mL of solution contains 100 mg of elemental iron as ferric derisomaltose in water for injection, hydrochloric acid and sodium hydroxide may be used to adjust pH.

12 CLINICAL PHARMACOLOGY

12.1 Mechanism of Action

Ferric derisomaltose is a complex of iron (III) hydroxide and derisomaltose, an iron carbohydrate oligosaccharide that releases iron. Iron binds to transferrin for transport to erythroid precursor cells to be incorporated into hemoglobin.

12.2 Pharmacodynamics

Serum ferritin peaks approximately 7 days after an intravenous dose of Monoferric and slowly returns to stable levels after about 4 weeks.

Cardiac Electrophysiology

Electrocardiogram (ECG) monitoring for QT prolongation was performed in a sub-study in 35 patients randomized to Monoferric in Trial 1. No large mean increase in QTc (i.e. >20 ms) interval was detected at the 1000 mg single dose of Monoferric.

12.3 Pharmacokinetics

The pharmacokinetics of total iron (derisomaltose-bound plus transferrin-bound iron) were evaluated in adult patients with IDA.

After a single dose of Monoferric, maximum concentration (Cmax) and area under the concentration time curve (AUC) of serum total iron increased approximately proportionally over the 100 to 1000 mg dose range. After a 1000 mg single dose, the Cmax and AUCinf of total iron (geometric mean and CV%) of serum total iron were 408 (10.5) μg/mL and 17730 (22.1) μg.h /mL.

Distribution

Circulating iron is removed from the plasma by cells of the reticuloendothelial system. The iron is bound to the available protein moieties to form hemosiderin or ferritin, the physiological storage forms of iron, or to a lesser extent, to the transport molecule transferrin.

Elimination

After a single 1000 mg Monoferric dose, the mean (CV%) half-life of serum total iron is 27 (13.3%) hr.

Excretion

Due to the size of the complex, Monoferric is not excreted via the kidneys. Small quantities of iron are excreted in urine and feces.

13 NONCLINICAL TOXICOLOGY

13.1 Carcinogenesis, Mutagenesis, Impairment of Fertility

Carcinogenicity studies have not been conducted.

Iron oligosaccharide, an earlier formulation of ferric derisomaltose, was not genotoxic in an in vitro bacterial reverse mutation assay, an in vitro chromosomal aberrations test and an in vivo mouse micronucleus assay.

In a combined fertility and embryo-fetal development study in rats, ferric derisomaltose was administered intravenously to male rats 28 days prior to mating and through cohabitation and to female rats 14 days prior to cohabitation and through GD 17. Doses administered were 2, 6, or 19 mg Fe/kg/day in males and 3, 11, or 32 mg Fe/kg/day in females. There was no effect on male or female fertility in rats at up to 19 mg Fe/kg/day (approximately 0.2 times the MRHD of 1000 mg, based on BSA) in males and up to 32 mg Fe/kg/day (approximately 0.3 times the MRHD of 1000 mg based on BSA) in females.

14 CLINICAL STUDIES

The safety and efficacy of Monoferric for treatment of iron deficiency anemia (IDA) were evaluated in two randomized, open-label, actively-controlled clinical trials performed in a total of 3050 patients with IDA of different etiology. Trial 1 included patients with IDA who had intolerance to oral iron or who had had unsatisfactory response to oral iron or for whom there was a clinical need for rapid repletion of iron stores. Trial 2 included patients with IDA who had non-dialysis dependent chronic kidney disease (NDD-CKD). In these two 8-Week trials, patients were randomized 2:1 to treatment with Monoferric or iron sucrose. Monoferric was intravenously administered as a single dose of 1000 mg.

Iron Deficiency Anemia in Patients Who Had Intolerance to Oral Iron or Who Had Unsatisfactory Response to Oral Iron

In Trial 1 (NCT02940886) 1512 adult patients with IDA caused by different etiologies, who had documented intolerance or lack of response to oral iron or screening hemoglobin (Hb) measurement sufficiently low to require repletion of iron stores were randomized in a 2:1 ratio to treatment with Monoferric or iron sucrose. Adult patients aged ≥18 years with baseline Hb ≤11 g/dL, TSAT <20 %, and s-ferritin <100 ng/mL were eligible for enrollment. The median age of patients was 44 years (range 18-91) and 89 % were women.

The efficacy of Monoferric was established based upon the change in Hb from baseline to week 8. Non-inferiority was demonstrated for change in Hb from baseline to Week 8 (Table 2).

Table 2. Change in Hemoglobin Endpoints in Trial 1
Trial 1 | Monoferric N = 1009 | Iron sucrose N = 503 | Difference
Mean change in Hb from Baseline to Week 8 Mean [Least square mean] (95% CI), g/dL (Primary endpoint) | 2.49 (2.41;2.56) | 2.49 (2.38;2.59) | Estimate [The estimate is from a mixed model for repeated measures with treatment, week, treatment-by-week and stratum as fixed effects and baseline Hb and baseline-by-week as covariates.] : 0.00 (95% CI -0.13;0.13) Non-inferiority confirmed

Iron Deficiency Anemia in Patients with Non-Hemodialysis Dependent Chronic Kidney Disease (NDD-CKD)

Trial 2 (NCT02940860) was a randomized controlled trial in 1538 patients with NDD-CKD who were randomized in a 2:1 ratio to treatment with Monoferric or iron sucrose respectively. Adult patients aged ≥18 years with Hb ≤11 g/dL, s-ferritin ≤100 ng/mL (or ≤300 ng/mL if TSAT ≤30%), chronic renal impairment with eGFR between 15-59 mL/min, and either no ESAs or ESAs at a stable dose (+/-20 %) for 4 weeks before randomization were eligible for enrollment. The median age of patients was 69 years (range 25-97), 63% were female.

The efficacy of Monoferric was established based upon the demonstration of non-inferiority for change in hemoglobin from baseline to Week 8 (Table 3).

Table 3. Change in Hemoglobin Endpoints in Trial 2
Trial 2 | Monoferric N = 1027 | Iron sucrose N = 511 | Difference
Mean change in Hb from Baseline to Week 8 Mean [Least square mean] (95% CI), g/dL (Primary endpoint) | 1.22 (1.14;1.31) | 1.14 (1.03;1.26) | Estimate [The estimate is from a mixed model for repeated measures with treatment, week, treatment-by-week and stratum as fixed effects and baseline Hb and baseline-by-week as covariates.] : 0.08 (95% CI -0.06;0.23) Non-inferiority confirmed

16 HOW SUPPLIED/STORAGE AND HANDLING

16.1 How Supplied

Monoferric injection is a sterile, dark brown, non-transparent aqueous solution supplied in cartons as single-dose vials (10 mL, 5 mL or 1 mL) in the following configurations:

Vial size | Number of vials per carton | NDC
1,000 mg/10 mL | 1 | 73594-9310-1
500 mg/5 mL | 1 | 73594-9305-1
100 mg/mL | 5 | 73594-9301-2

16.2 Storage and Handling

Store at 20° to 25°C (68° to 77°F); excursions permitted to 15° to 30°C (59° to 86°F). See the USP controlled room temperature.

Do not freeze.

When added to an infusion bag containing 0.9% Sodium Chloride Injection, USP, Monoferric solution may be stored for up to 8 hours at room temperature.

17 PATIENT COUNSELING INFORMATION

Advise the patient to read the FDA-approved patient labeling (Patient Information).

Prior History of Allergies to Parenteral Iron Products

Question patients regarding any prior history of reactions to parenteral iron products (see Warnings and Precautions (5.1)) .

Hypersensitivity Reactions

Advise patients to report any signs and symptoms of hypersensitivity that may develop during and following Monoferric administration, such as rash, itching, dizziness, lightheadedness, swelling and breathing problems (see Warnings and Precautions (5.1)) .

Distributed by: Pharmacosmos Therapeutics Inc., Morristown, NJ 07960
Monoferric is manufactured under license from Pharmacosmos A/S, Denmark

Patient Information
MONOFERRIC (mon-oh-fer-ik)
(ferric derisomaltose)
Injection

What is MONOFERRIC?
MONOFERRIC is a prescription iron replacement medicine used to treat iron deficiency anemia in adults who have:

- intolerance to oral iron or who have not responded well to treatment with oral iron
- non-dialysis dependent chronic kidney disease

It is not known if MONOFERRIC is safe and effective for use in children less than 18 years old.

Who should not receive MONOFERRIC?
Do not receive MONOFERRIC if you are allergic to ferric derisomaltose or any of the ingredients in MONOFERRIC.
See the end of this leaflet for a complete list of ingredients in MONOFERRIC.

Before receiving MONOFERRIC, tell your healthcare provider about all of your medical conditions, including if you:

- have had an allergic reaction to IV iron
- are pregnant or plan to become pregnant. It is not known if MONOFERRIC will harm your unborn baby.
- are breastfeeding or plan to breastfeed. MONOFERRIC passes into your breast milk and may harm your baby. Talk to your healthcare provider about the best way to feed your baby during treatment with MONOFERRIC.

Tell your healthcare provider about all the medicines you take, including prescription and over-the-counter medicines, vitamins, and herbal supplements.
Know the medicines you take. Keep a list of them to show to your healthcare provider and pharmacist when you get a new medicine.

How will I receive MONOFERRIC?
MONOFERRIC is given into your vein (intravenously) by your healthcare provider over at least 20 minutes.

What are the possible side effects of MONOFERRIC?
MONOFERRIC may cause serious side effects, including:

- Allergic (hypersensitivity) reactions. Serious life-threatening allergic reactions have happened in people who receive MONOFERRIC. Symptoms of an allergic reaction including rash, itching, hives, dizziness, lightheadedness, breathing problems and low blood pressure have also happened during treatment with MONOFERRIC. Tell your healthcare provider right away if you develop any of the above symptoms of a serious allergic reaction or if you have ever had any unusual or allergic reaction to any IV iron in the past.
- Too much iron stored in your body (iron overload). Your healthcare provider should check the iron level in your blood before you start and during treatment with MONOFERRIC.

The most common side effects of MONOFERRIC include rash and nausea.
These are not all the possible side effects of MONOFERRIC.
Call your doctor for medical advice about side effects. You may report side effects to FDA at 1-800-FDA-1088.

General information about MONOFERRIC
Medicines are sometimes prescribed for purposes other than those listed in a Patient Information leaflet. You can ask your pharmacist or healthcare provider for information about MONOFERRIC that is written for health professionals.

What are the ingredients in MONOFERRIC?
Active ingredient: ferric derisomaltose
Inactive ingredients: water for injection
Manufactured under license from Pharmacosmos A/S, Denmark
Distributed by: Pharmacosmos Therapeutics Inc., Morristown, NJ 07960
For more information go to www.pharmacosmos.com or call 1-888-828-0655 .

8This Patient Information has been approved by the U.S. Food and Drug Administration.

Issued: 02/2020

PRINCIPAL DISPLAY PANEL - 100 mg/mL Vial Box

PHARMACOSMOS

MonoFerric®
(ferric derisomaltose) injection

100 mg / mL

FOR INTRAVENOUS INFUSION AFTER DILUTION
Discard unused portion
Sterile
Rx Only

5 x 1 mL Single-Dose Vials

PRINCIPAL DISPLAY PANEL - 500 mg/5 mL Vial Box

MonoFerric®
(ferric derisomaltose)
injection

500 mg / 5 mL
(100 mg/mL)

FOR INTRAVENOUS INFUSION
AFTER DILUTION
One single-dose vial
Discard unused portion
Sterile

Rx Only

PRINCIPAL DISPLAY PANEL - 1000 mg/10 mL Vial Box

MonoFerric®
(ferric derisomaltose)
injection

1000 mg / 10 mL
(100 mg/mL)

FOR INTRAVENOUS INFUSION
AFTER DILUTION
One single-dose vial
Discard unused portion
Sterile

Rx Only

PRINCIPAL DISPLAY PANEL- 10 mL Vial Single Dose

MonoFerric®
(ferric derisomaltose)
injection

1000 mg / 10 mL
(100 mg/mL)

FOR INTRAVENOUS INFUSION
AFTER DILUTION
One single-dose vial
Discard unused portion
Sterile

Rx Only